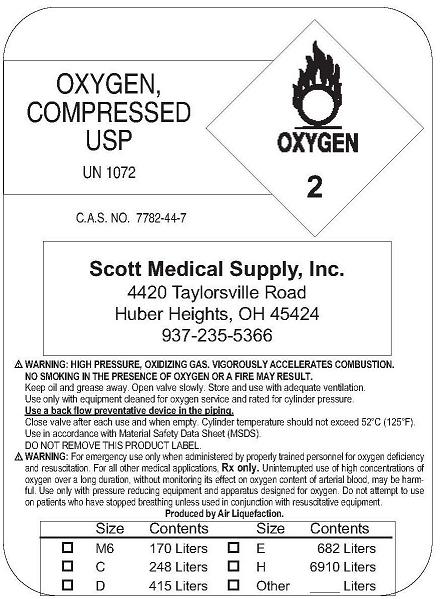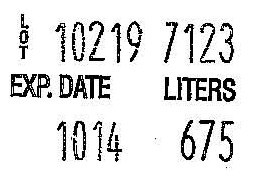 DRUG LABEL: Oxygen
NDC: 67490-0001 | Form: GAS
Manufacturer: Scott Medical Supply Inc. 
Category: prescription | Type: HUMAN PRESCRIPTION DRUG LABEL
Date: 20091112

ACTIVE INGREDIENTS: Oxygen 99 L/100 L

Oxygen